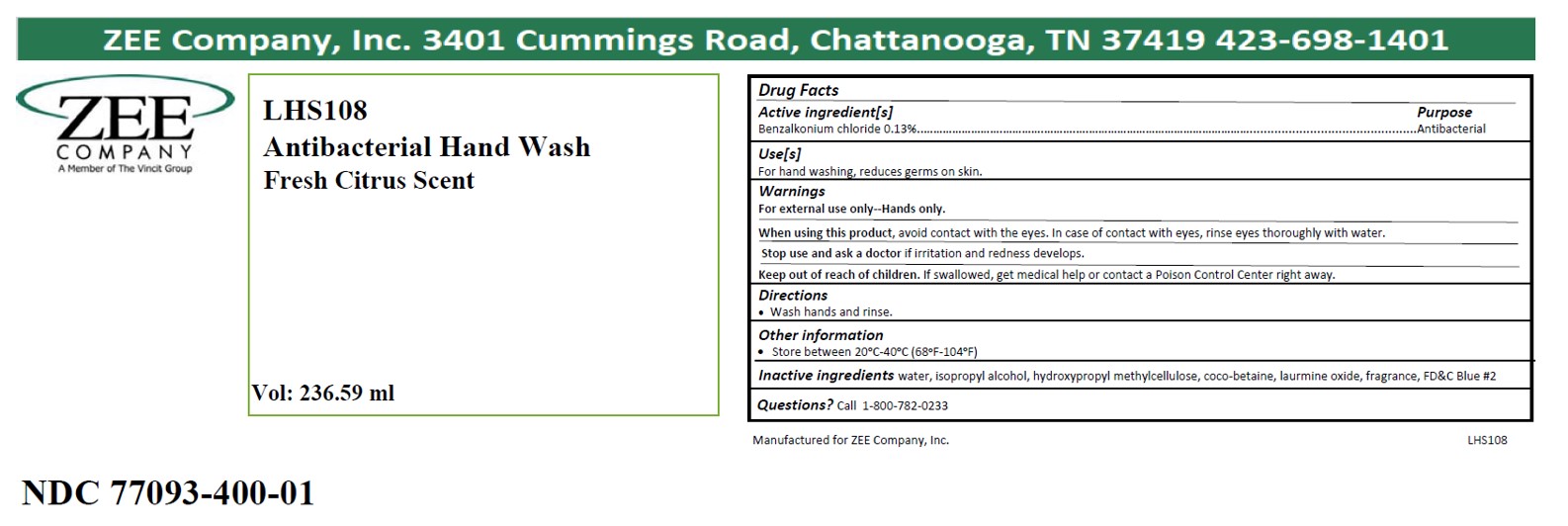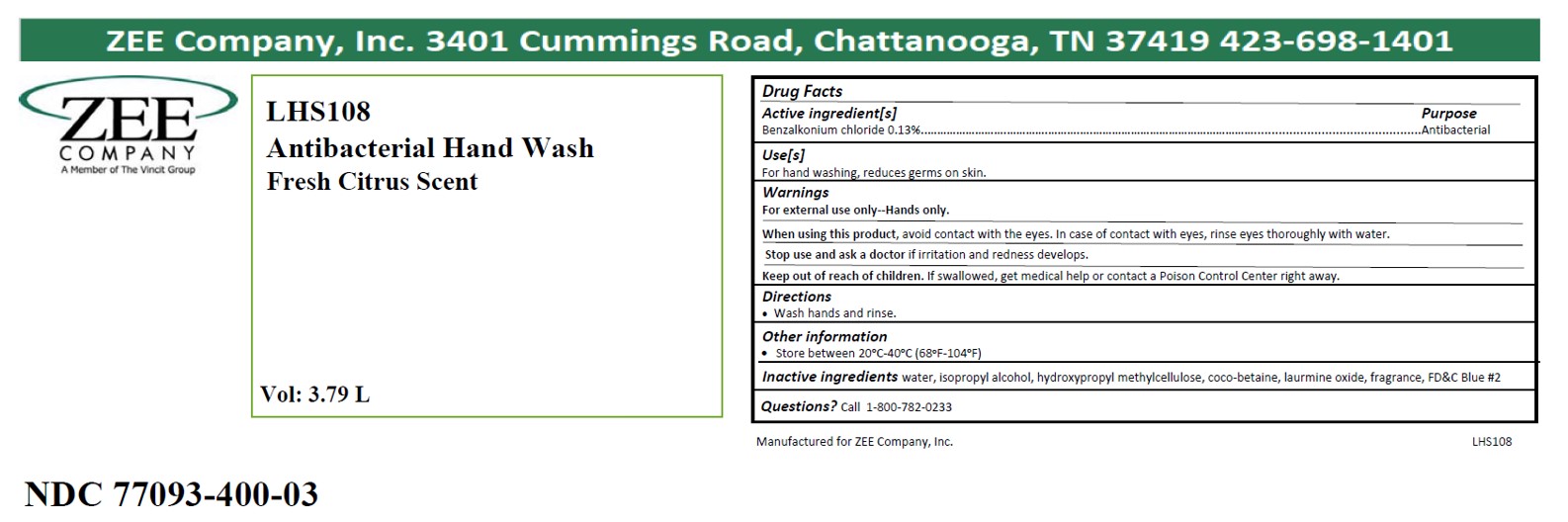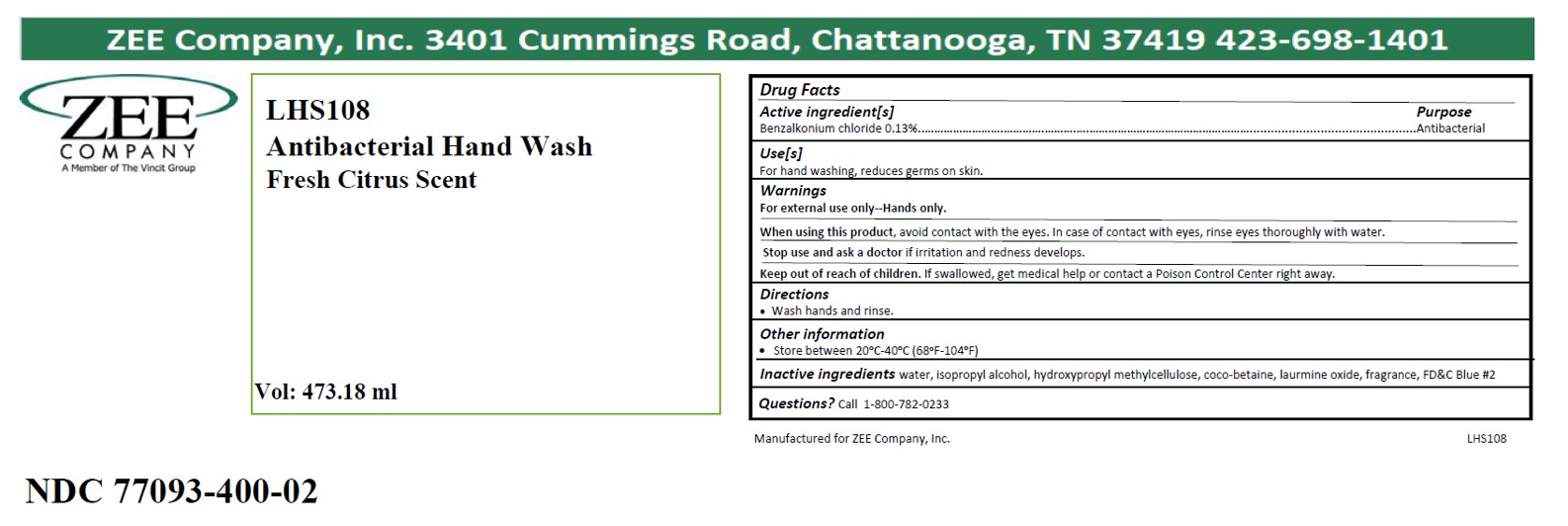 DRUG LABEL: LHS108
NDC: 77093-400 | Form: LIQUID
Manufacturer: Vincit Zee Company
Category: otc | Type: HUMAN OTC DRUG LABEL
Date: 20200728

ACTIVE INGREDIENTS: BENZALKONIUM CHLORIDE 0.13 g/100 mL
INACTIVE INGREDIENTS: COCO-BETAINE; LAURAMINE OXIDE; HYPROMELLOSES; WATER; ISOPROPYL ALCOHOL

LHS108

active ingredient

Benzalkonium Chloride

purpose

Antibacterial

INDICATIONS AND USAGE

Avoid contact with the eyes. In case of contact with eyes, rinse eyes thoroughly with water.

WARNINGS

For external use only - Hands only.

WHEN USING

Avoid contact with the eyes. In case of contact with eyes, rinse eyes thoroughly with water.

Stop use and ask a doctor if irritation and redness develops.

Keep out of reach of children. If swallowed get medical help or contact a Poison Control Center right away.

DOSAGE AND ADMINISTRATION

Wash hands and rinse.

INACTIVE INGREDIENT

water, acrylates copolymer, glycerin, aminomethyl propanol, hydroxypropyl methylcellulose, fragrance

LHS108 Product Labels

263.59 ml: NDC Code 77093-400-01

473.18 ml: NDC Code 77093-400-02

3785ml : NDC Code 77093-400-03